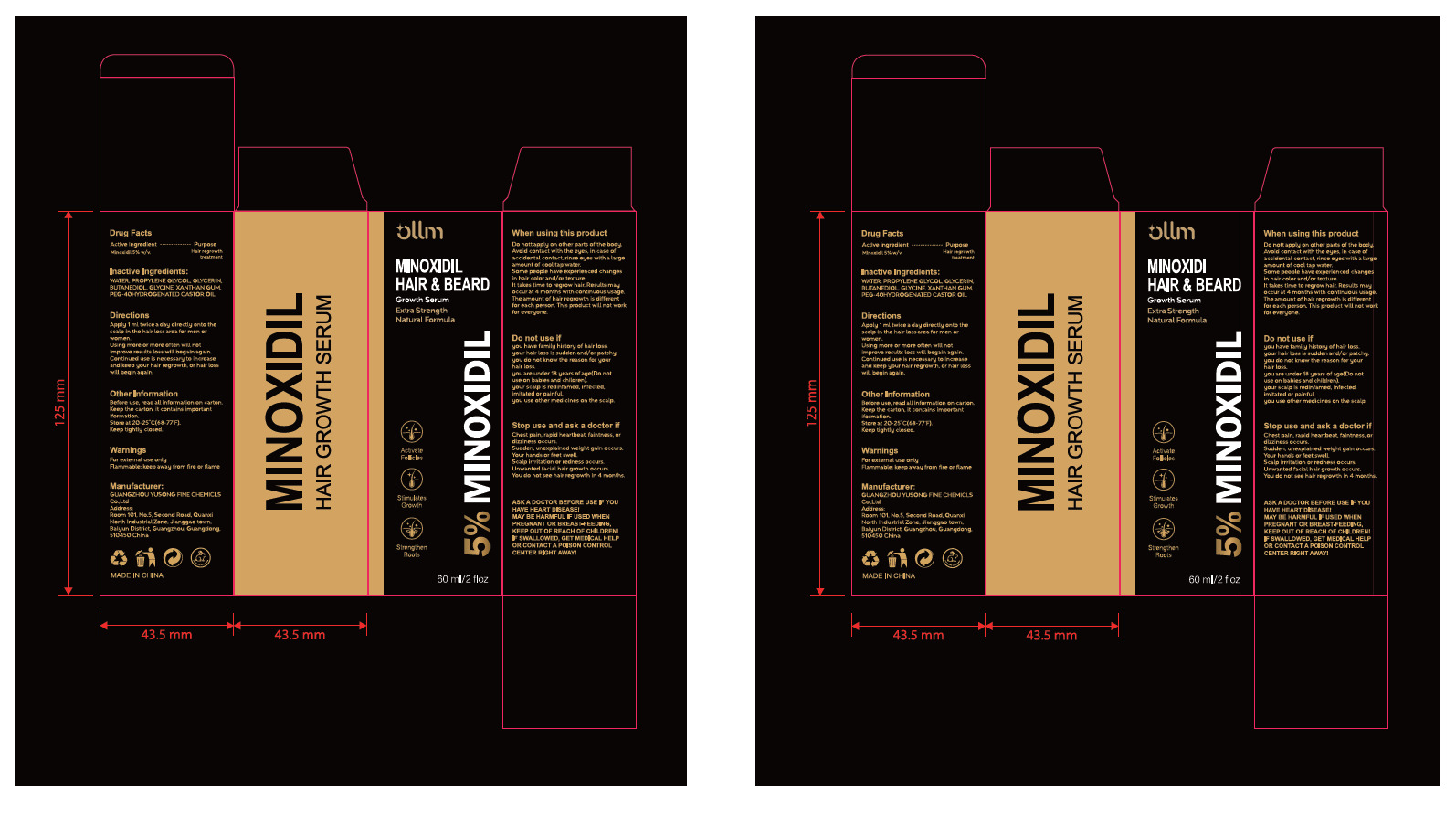 DRUG LABEL: Ollm 5% MINOXIDIL Growth Serum
NDC: 84558-011 | Form: LIQUID
Manufacturer: GUANGZHOU YUSONG FINE CHEMICLS Co., Ltd
Category: otc | Type: HUMAN OTC DRUG LABEL
Date: 20250721

ACTIVE INGREDIENTS: MINOXIDIL 5 g/100 mL
INACTIVE INGREDIENTS: PEG-40 HYDROGENATED CASTOR OIL; GLYCINE; WATER; PROPYLENE GLYCOL; GLYCERIN; BUTANEDIOL (MIXED ISOMERS); XANTHAN GUM

84558-011

Active Ingredient(s)

Minoxidil 5%

Purpose

Hair regrowth
treatment

Use

Apply 1 ml twice a day directly onto the scalp in the hair loss area for men or women.

Warnings

For external use only
Flammable: keep away from fire or flame

Do not use

you have family history of hair loss.
your hair loss is sudden and/ or patchy.
you do not know the reason for your hair loss.
you are under 18 years of age(Do not use on babies and children).
your scalp is redinfamed, infected, imitated or painful.
you use other medicines on the scalp.

WHEN USING

Do nott apply on other parts of the body. Avoid contact with the eyes, in case of accidental contact, rinse eyes with a large
amount of cool tap water. Some people have experienced changes in hair color and/ or texture.
It takes time to regrow hair. Results may occur at 4 months with continuous usage. The amount of hair regrowth is different
for each person. This product will not work for everyone.

STOP USE

Chest pain, rapid heartbeat, faintness, or dizziness occurs.
Sudden, unexpiained weight gain occurs.

Your hands or feet swell.
Scalp rrritation or redness occurs.
Unwanted facial hair growth occurs.
You do not see hair regrowth in 4 months.

Keep out of reach of children. If swallowed, get medical help or contact a Poison Control Center
right away

Directions

Apply 1 ml twice a day directly onto the scalp in the hair loss area for men or women.
Using more or more often will not improve results loss will begain again.
Continued use is necessary to increase and keep your hair regrowth, or hair loss will begin again.

Other information

Before use, read all information on carton. Keep the carton, it contains important iformation.
Store at 20-25°C(68-77'F). Keep tightly closed.

Inactive ingredients

WATER, PROPYL .ENE GLYCOL, GLYCERIN, BUTANEDIOL, GLYCINE, XANTHAN GUM,
PEG- 40H HYDROGENATED CASTOR OIL